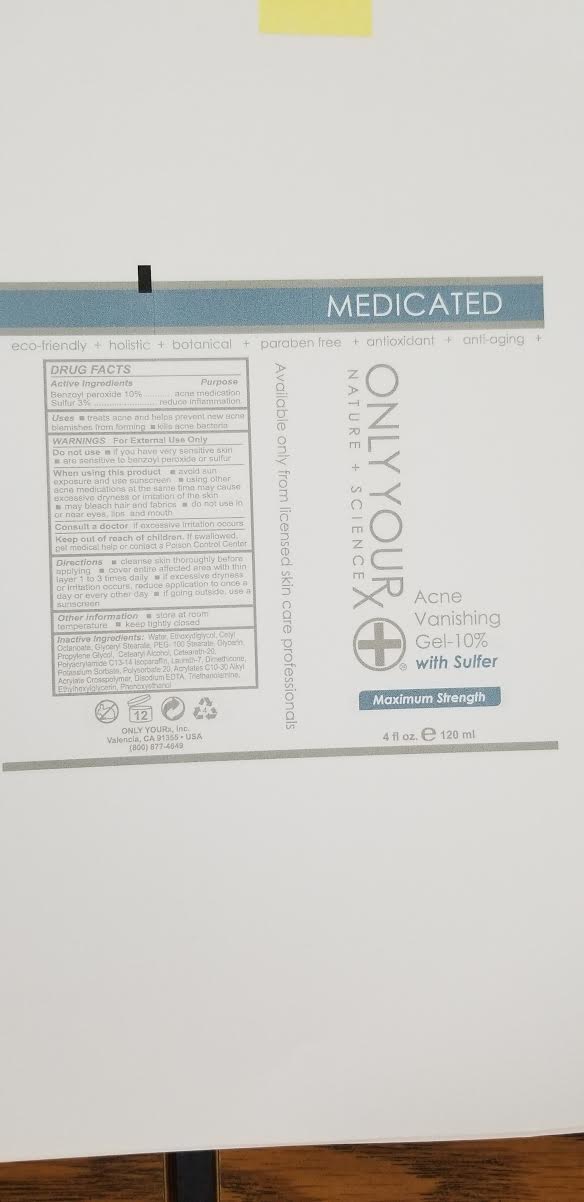 DRUG LABEL: Acne Vanishing Gel- 10% with Sulfur
NDC: 70367-003 | Form: GEL
Manufacturer: Only Yourx, Inc.
Category: otc | Type: HUMAN OTC DRUG LABEL
Date: 20200123

ACTIVE INGREDIENTS: BENZOYL PEROXIDE 10 g/100 mL; SULFUR 3 g/100 mL
INACTIVE INGREDIENTS: CETEARETH-22; MAGNESIUM DISODIUM EDTA; AMINOMETHYLPROPANOL; PHENOXYETHANOL; CETYL OCTACOSANOATE; GLYCERYL STEARATE SE; LAURETH-7; ETHYLHEXYLGLYCERIN; PROPYLENE GLYCOL 1-(2-METHYLBUTYRATE); DIMETHICONE; POTASSIUM SORBATE; POLYSORBATE 20; C13-14 ISOPARAFFIN; GLYCERIN; PEG-100 STEARATE

WARNINGS: For External Use Only

Active Ingredients:

Benzoyl Peroxide 10%

Sulfur 3%

INDICATIONS AND USAGE

Treats acne and helps prevent new blemishes from forming

Kills acne bacteria

Do Not Use: if you have very sensitive skin

are sensitive to benzoyl peroxide or sulfur

When using this product

avoid sun exposure and use sunscreen

using other acne medications at the same time may cause excessive dryness or irritation of the skin

may bleach hair and fabrics

do not use in or near eyes, lips and mouth

Consult a doctor if excessive irritation occurs

Keep out of reach of children. If swallowed, get medical help or contact a Poison Control Center

Directions:

cleanse skin thoroughly before applying

cover entire affected area with thin layer 1 to 3 times daily

if excessive dryness or irritation occurs, reduce application to once a day or every oter day
if going outside, use a sunscreen

Other information

store at room temperature

keep tightly closed

Inactive Ingredients:

Water, Ethoxydiglycol, Cetyl Octanoate, Glyceryl Stearate, APEG-100 Stearate, Glycerin, Propylene Glycol, Cetearyl Alcohol, Ceteareth-20, Polyacrylamide C13-14 Isoparaffin, Laureth-7, Dimethicone, Potassium Sorbate, Polysorbate 20, Acrylates C10-30 Alkyl Acrylate Crosspolymer, Disodium EDTA, Triethanolamine, Ethylhexylglycerin, Phenoxyethanol

PURPOSE

To treat acne and reduce inflammation